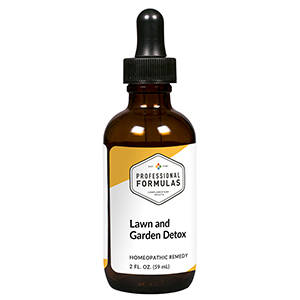 DRUG LABEL: Lawn and Garden Detox
NDC: 63083-6026 | Form: LIQUID
Manufacturer: Professional Complementary Health Formulas
Category: homeopathic | Type: HUMAN OTC DRUG LABEL
Date: 20190815

ACTIVE INGREDIENTS: 2-MERCAPTOETHANOL 30 [hp_X]/59 mL; CARBON MONOXIDE 30 [hp_X]/59 mL; BOROSILICATE GLASS 30 [hp_X]/59 mL; POLYVINYL ALCOHOL, UNSPECIFIED 30 [hp_X]/59 mL; MCPA 30 [hp_X]/59 mL; ETHYL BUTYLACETYLAMINOPROPIONATE 30 [hp_X]/59 mL; TRALOMETHRIN 30 [hp_X]/59 mL; HOPS OIL 30 [hp_X]/59 mL; TITANIUM DIOXIDE 30 [hp_X]/59 mL; LIQUID PETROLEUM 30 [hp_X]/59 mL
INACTIVE INGREDIENTS: ALCOHOL; WATER

X26

ACTIVE INGREDIENTS

all the following at 30X, 60X:
Antifreeze
Carbon monoxide
Fiberglass
Glues
Herbicides
Insect repellents
Insecticides
Oils
Paints
Pet insecticides
Petroleum

QUESTIONS

Professional Formulas

PO Box 2034 Lake Oswego, OR 97035

INDICATIONS

For the temporary relief of eye, nose, or throat irritation, occasional headache, coughing, shortness of breath, fatigue, or red, itchy, irritated skin due to sensitivity to or exposure to yard maintenance chemicals or materials.*

PURPOSE

*Claims based on traditional homeopathic practice, not accepted medical evidence. Not FDA evaluated.

WARNINGS

In case of overdose, get medical help or contact a poison control center right away.

Keep out of the reach of children.

PREGNANCY OR BREAST FEEDING

If pregnant or breastfeeding, ask a healthcare professional before use.

DIRECTIONS

Place drops under tongue 30 minutes before/after meals. Adults and children 12 years and over: Take 10 drops up to 3 times per day. Consult a physician for use in children under 12 years of age.

OTHER INFORMATION

Tamper resistant. If seal is broken, do not use. After opening, close container tightly and store at room temperature away from heat.

INACTIVE INGREDIENTS

20% ethanol, purified water.

LABEL

Est 1985

Professional Formulas

Complementary Health

Lawn and Garden Detox

Homeopathic Remedy

2 FL. OZ. (59 mL)